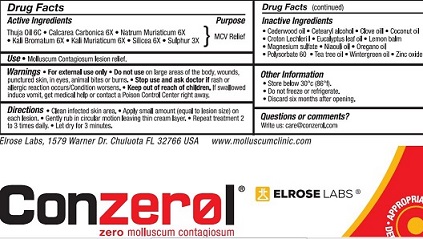 DRUG LABEL: Elrose Labs
NDC: 70223-001 | Form: CREAM
Manufacturer: Elroselabs Inc.
Category: homeopathic | Type: HUMAN OTC DRUG LABEL
Date: 20151217

ACTIVE INGREDIENTS: SILICON DIOXIDE 6 mg/28.3 mg; OYSTER SHELL CALCIUM CARBONATE, CRUDE 6 mg/28.3 mg; SODIUM CHLORIDE 6 [hp_X]/28.3 mg; POTASSIUM CHLORIDE 6 mg/28.3 mg; POTASSIUM BROMIDE 6 mg/28.3 mg
INACTIVE INGREDIENTS: CROTON LECHLERI WHOLE; WHITE WAX; POLYSORBATE 60; MAGNESIUM SULFATE; GLYCERIN; Zinc Oxide; DIMETHYL ISOSORBIDE; TEA TREE OIL; CLOVE OIL; METHYL SALICYLATE; OREGANO LEAF OIL; LEMON BALM OIL; JUNIPERUS VIRGINIANA OIL; NIAOULI OIL; EUCALYPTUS OIL; COCONUT OIL

WARNINGS

For external use only. do not use on large areas, on wounds, punctured skin, in eyes, animal bites or burns. Stop use if rash or allergic reaction occurs/ condition worsens.

ACTIVE INGREDIENT

SILICEA

CALCAREA CARBONICA

THUJA OIL

NATRUM MURIATICUM

KALI BROMATUM

SULPHAR

KALI MURIATICUM

Keep out of reach of children. If swallowed induce vomit. Get medical help or contact a poison control center right away.

PURPOSE

MCV Relief

DOSAGE AND ADMINISTRATION

Clean infected skin area.Apply a small amount(equal to lesion size) on each lesion. Gently rub in circular motion leaving thin cream layer.Repeat treatment 2 to 3 times daily. Let dry for 3 minutes.

INDICATIONS AND USAGE

Molluscum Contagiosum Lesion Relief

INACTIVE INGREDIENT

Croton Lechleri
Emulsifying Wax NF
Polysorbate 60
Magnesium Sulfate
Vegetable Glycerine
Zinc Oxide
Dimethyl Isosorbide
Tea Tree Oil
Colve Oil
Wintergreen Oil
Oragano Oil
Lemon Balm Oil
Cedarwood Oil
Niaouli Oil
Eucalyptus Leaf Oil
Coconut Oil